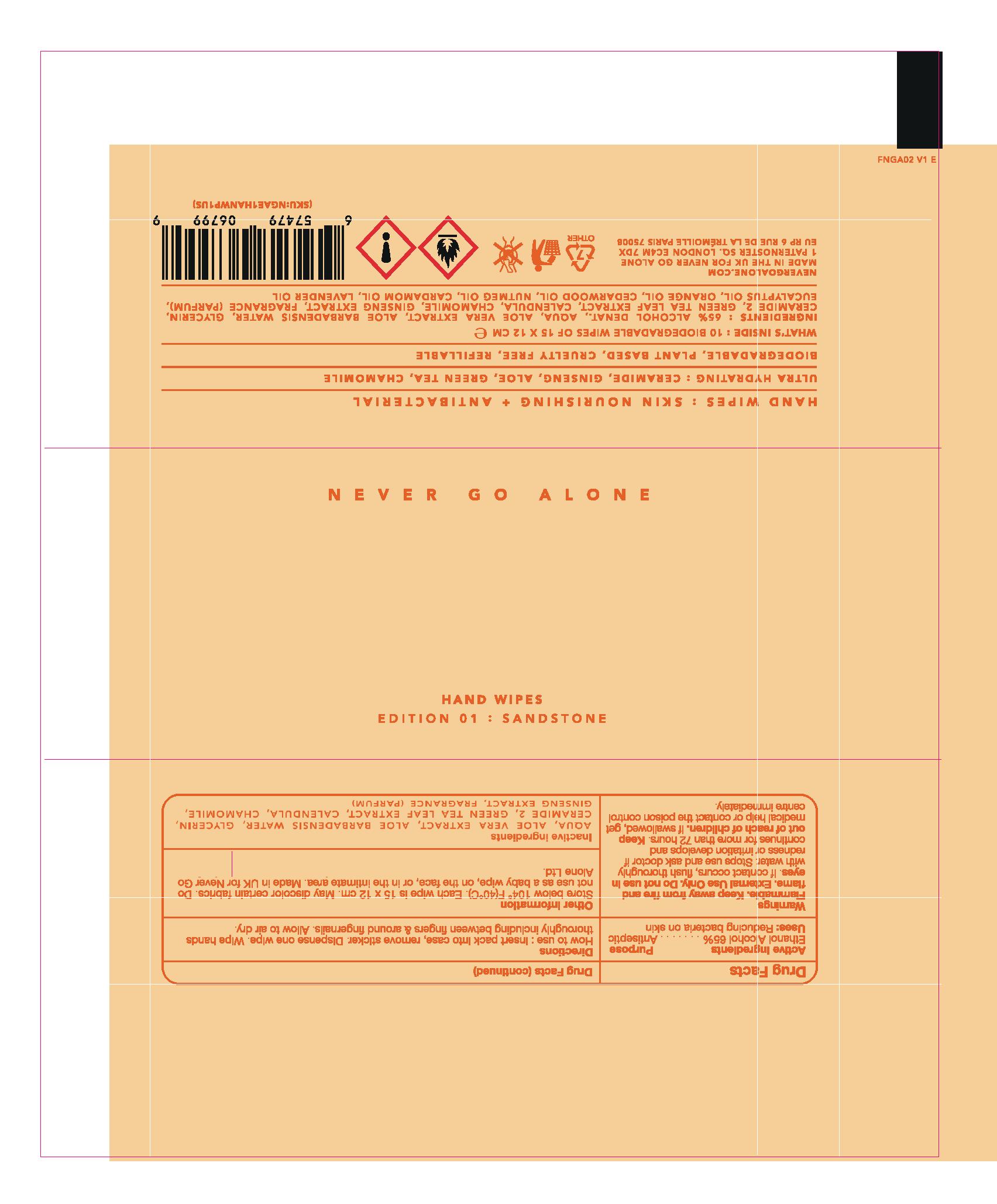 DRUG LABEL: NGA ALCOHOL WIPES SANDSTONE
NDC: 83732-0110 | Form: SWAB
Manufacturer: NEVER GO ALONE
Category: otc | Type: HUMAN OTC DRUG LABEL
Date: 20231005

ACTIVE INGREDIENTS: ALCOHOL 17.55 g/27 g
INACTIVE INGREDIENTS: CALENDULA OFFICINALIS FLOWER 0.02 g/27 g; ASIAN GINSENG 0.01 g/27 g; GREEN TEA LEAF 0.02 g/27 g; GLYCERIN 0.3 g/27 g; WATER 8.21 g/27 g; PALMITOYL MYRISTYL SERINATE 0.02 g/27 g; ALOE VERA LEAF 0.6 g/27 g; CHAMOMILE 0.01 g/27 g; FRAGRANCE 13576 0.26 g/27 g

NEVER GO ALONE - HAND WIPES - EDITION 01 : SANDSTONE

Hand sanitizer (65%(w/w) denatured ethanol in an aqueous solution):

- Manufactured using United States Pharmacopoeia (USP) grade ingredients including USP water.

- The alcohol (ethanol) is (USP or Food Chemical Codex (FCC) grade), and is denatured according to Alcohol & Tobacco Tax and Trade Bureau regulations in 27 CFR part 20.

ACTIVE INGREDIENT

Ethanol Alcohol 65%

PURPOSE

Antiseptic

USES

Uses: Reducing Bacteria on skin

WARNINGS

Flammable. Keep away from fire and flame. External use only. Do not use in eyes. If contact occurs, flush thoroughly with water. Stop use and ask doctor if redness or irritation develops and continues for more than 72 hours. Keep out of reach of children. If swallowed, get medical help or contact the poison control centre immediately.

Keep out of reach of children.

Directions

How to Use: insert pack into case, remove sticker. Dispense one wipe. WIpe hands thoroughly including between fingers & around fingerails. Allow to air dry.

DOSAGE AND ADMINISTRATION

Dispense one wipe. Wipe hands thoroughly including between fingers & around fingernails. Allow to Air dry.

Other Information

Store below 104°F(40°C). Each wipe is 15 x 12 cm. May discolour certain fabrics. Do not use as a baby wipe, on the face, or in the intimate area. Made in UK for Never Go Alone Ltd.

INACTIVE INGREDIENT

AQUA, ALOE VERA EXTRACT (ALOE BARDANENSIS WATER), GLYCERIN, CERAMIDE 2, GREEN TEA LEAF EXTRACT, CALENDULA, CHAMOMILE, GINSENG EXTRACT, FRAGRANCE (PARFUM)

PACKAGE LABEL

10 wipes; 83732-0110-1